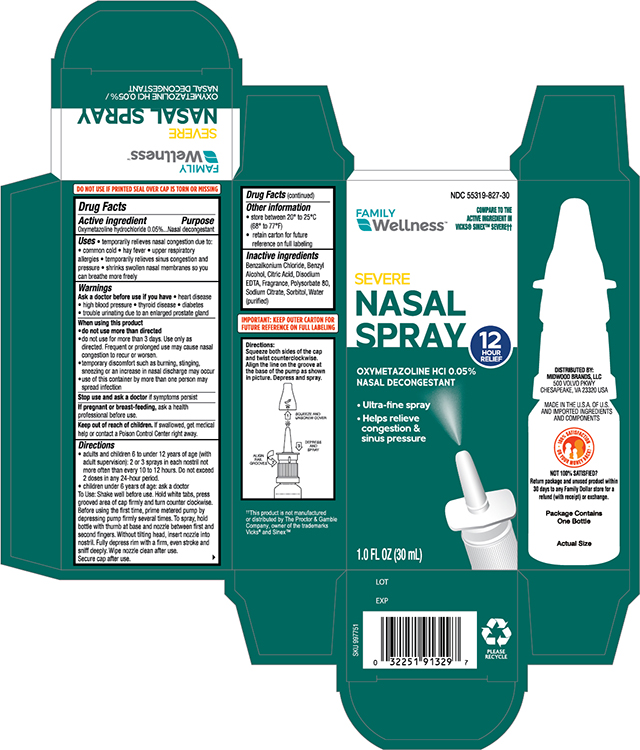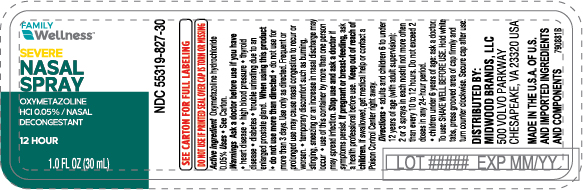 DRUG LABEL: Family Wellness Oxymetazoline Sinus Severe
NDC: 55319-827 | Form: SPRAY
Manufacturer: FAMILY DOLLAR (Family Wellness)
Category: otc | Type: HUMAN OTC DRUG LABEL
Date: 20241121

ACTIVE INGREDIENTS: OXYMETAZOLINE HYDROCHLORIDE 50 mg/100 mL
INACTIVE INGREDIENTS: BENZALKONIUM CHLORIDE; BENZYL ALCOHOL; CITRIC ACID ACETATE; EDETATE DISODIUM ANHYDROUS; POLYSORBATE 80; SODIUM CITRATE; SORBITOL; WATER

Family Wellness Nasal Spray Sinus Severe

Drug Facts

Active Ingredient
Oxymetazoline Hydrochloride 0.05%

Purpose

Nasal Decongestant

Uses

Tempoarily relieves nasal congestion due to:

- common cold
- hay fever
- upper respirtory allergies
- temporaily relieves sinus congestion and pressure
- Shrinks swollen membranes so you can breathe more freely

Ask a Doctor before use if you have

- heart diease
- high blood pressure
- diabetes
- thyiod diease
- trouble urinating due to enlarged rostate gland.

When using this product

- Do not use more than directed
- do not use for more than three days, Use only as directed. Frequent or prolonged use may cause nasal congestion to recur or worsen.
- temporary discomfort such as burning ,stinging, sneezing or an increase in nasal discharge may occur.
- use of this container by more than one person may spread infection.

stop use and ask a doctor if

symptoms persist.

if pregnant or breast-feeding

ask a health professional before use.

Keep out of the reach of children

if swallowed, get medical help or contact a Poison Control Center right away.

Directions

- Adults and children 6 to under 12 years of age (with adult supervision):2 or 3 sprays in each nostril not more than every 10 to 12 hours. Do not exceed 2 doses in any 24-hour period.
- Children under 6 years of age consult a doctor.
- Before using for the first time, remove the protective cap form the tip and prime the pump by depressing pump firmly several times. To spray, hold bottle with thumb at base and nozzle between first and second fingers. Without tilting head, insert nozzle into nostrile. Fully depress rim with a firm and even stroke, and sniff deeply.
  Wipe nozzle clean after use.

Other information

- store between 20° and 25°C (68° to 77°F)
- retain carton for future reference on full labeling

Inactive Ingredients

Benzalkonium Chloride, Benzyl Alcohol, Citric Acid Anhydrous, Disodium EDTA, Fragrance, Polysorbate 80, Sodium Citrate, Sorbitol, Water (Purified)

Principal Display Panel- Bottle

Family Wellness NDC 55319-827-30

Severe Nasal Spray

Oxymetazoline HCL 0.05%

Nasal Decongestant

1.0 FLOZ (30ml)

Principal Display panel -Carton

Family Wellness NDC 55319-827-30
Severe Nasal Spray

Oxymetazoline HCL 0.05%

Nasal Decongestant

1.0 FLOZ (30ml)